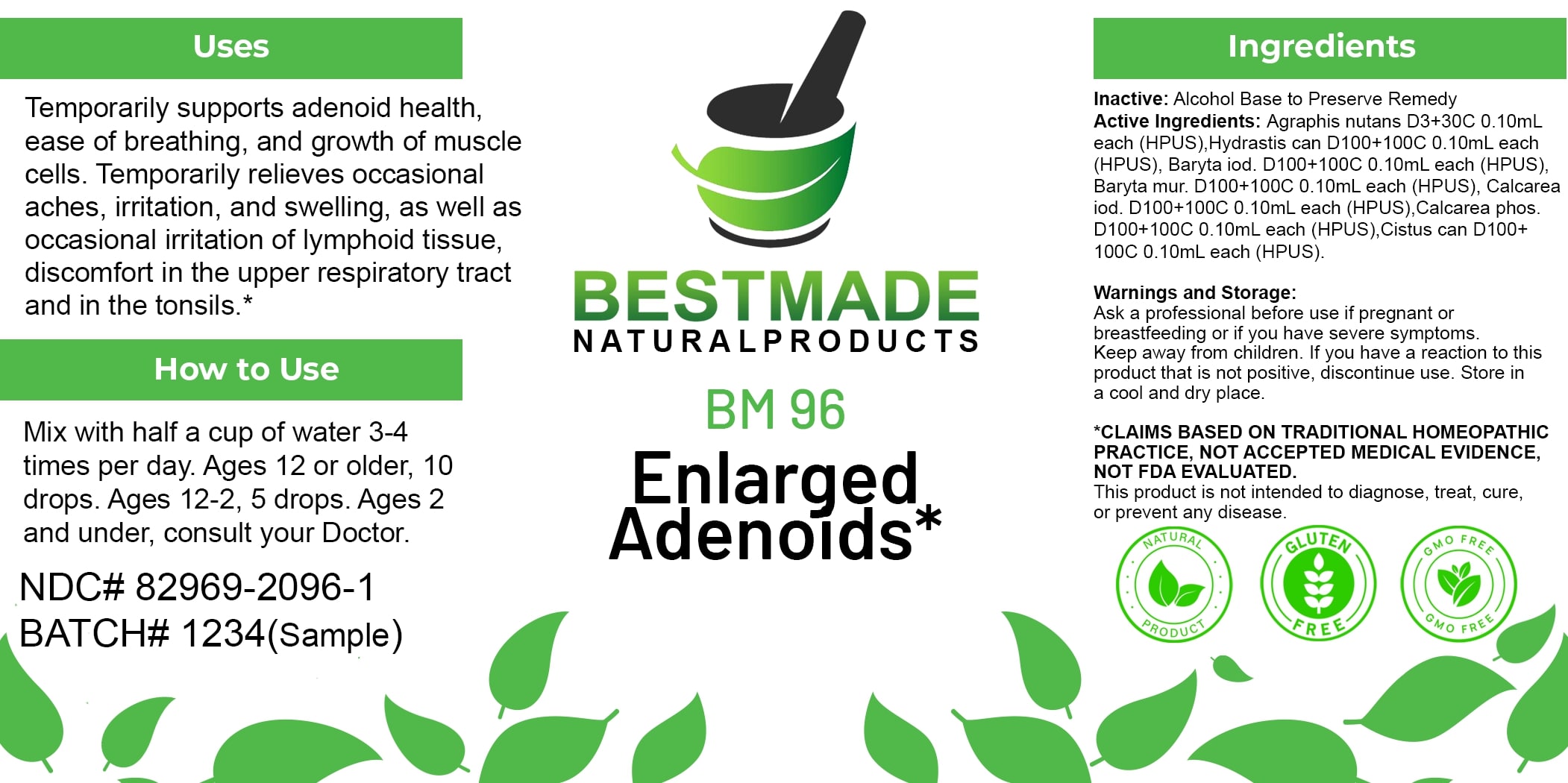 DRUG LABEL: Bestmade Natural Products BM96
NDC: 82969-2096 | Form: LIQUID
Manufacturer: Bestmade Natural Products
Category: homeopathic | Type: HUMAN OTC DRUG LABEL
Date: 20250205

ACTIVE INGREDIENTS: TRIBASIC CALCIUM PHOSPHATE 100 [hp_C]/100 [hp_C]; BARIUM CHLORIDE DIHYDRATE 100 [hp_C]/100 [hp_C]; BARIUM IODIDE 100 [hp_C]/100 [hp_C]; HYACINTHOIDES NON-SCRIPTA 30 [hp_C]/100 [hp_C]; CALCIUM IODIDE 100 [hp_C]/100 [hp_C]; HELIANTHEMUM CANADENSE 100 [hp_C]/100 [hp_C]; GOLDENSEAL 100 [hp_C]/100 [hp_C]
INACTIVE INGREDIENTS: ALCOHOL 100 [hp_C]/100 [hp_C]

BM96

DOSAGE AND ADMINISTRATION

How to Use

Mix with half a cup of water 3-4 times per day. Ages 12 or older, 10 drops. Ages 12-2, 5 drops. Ages 2 and under, consult your Doctor.

INACTIVE INGREDIENT

Ingredients

Inactive: Alcohol Base to Preserve Remedy

ACTIVE INGREDIENT

Active Ingredients: Agraphis nutans D3+30C 0.10mL each (HPUS), Hydrastis can D100+100C 0.10mL each (HPUS), Baryta iod. D100+100C 0.10mL each (HPUS), Baryta mur. D100+100C 0.10mL each (HPUS), Calcarea iod. D100+100C 0.10mL each (HPUS), Calcarea phos. D100+100C 0.10mL each (HPUS), Cistus can D100+100C 0.10mL each (HPUS).

Uses

Temporarily supports adenoid health, ease of breathing, and growth of muscle cells. Temporarily relieves occasional aches, irritation, and swelling, as well as occasional irritation of lymphoid tissue, discomfort in the upper respiratory tract and in the tonsils.*

*CLAIMS BASED ON TRADITIONAL HOMEOPATHIC PRACTICE, NOT ACCEPTED MEDICAL EVIDENCE, NOT FDA EVALUATED.

This product is not intended to diagnose, treat, cure, or prevent any disease.

Uses

Temporarily supports adenoid health, ease of breathing, and growth of muscle cells. Temporarily relieves occasional aches, irritation, and swelling, as well as occasional irritation of lymphoid tissue, discomfort in the upper respiratory tract and in the tonsils.*

*CLAIMS BASED ON TRADITIONAL HOMEOPATHIC PRACTICE, NOT ACCEPTED MEDICAL EVIDENCE, NOT FDA EVALUATED.

This product is not intended to diagnose, treat, cure, or prevent any disease.

KEEP OUT OF REACH OF CHILDREN

Warnings and Storage:

Ask a professional before use if pregnant or breastfeeding or if you have severe symptoms. Keep away from children. If you have a reaction to this product that is not positive, discontinue use. Store in a cool and dry place.

Warnings and Storage:

Ask a professional before use if pregnant or breastfeeding or if you have severe symptoms. Keep away from children. If you have a reaction to this product that is not positive, discontinue use. Store in a cool and dry place.

*CLAIMS BASED ON TRADITIONAL HOMEOPATHIC PRACTICE, NOT ACCEPTED MEDICAL EVIDENCE, NOT FDA EVALUATED.

This product is not intended to diagnose, treat, cure, or prevent any disease.

Entire package label